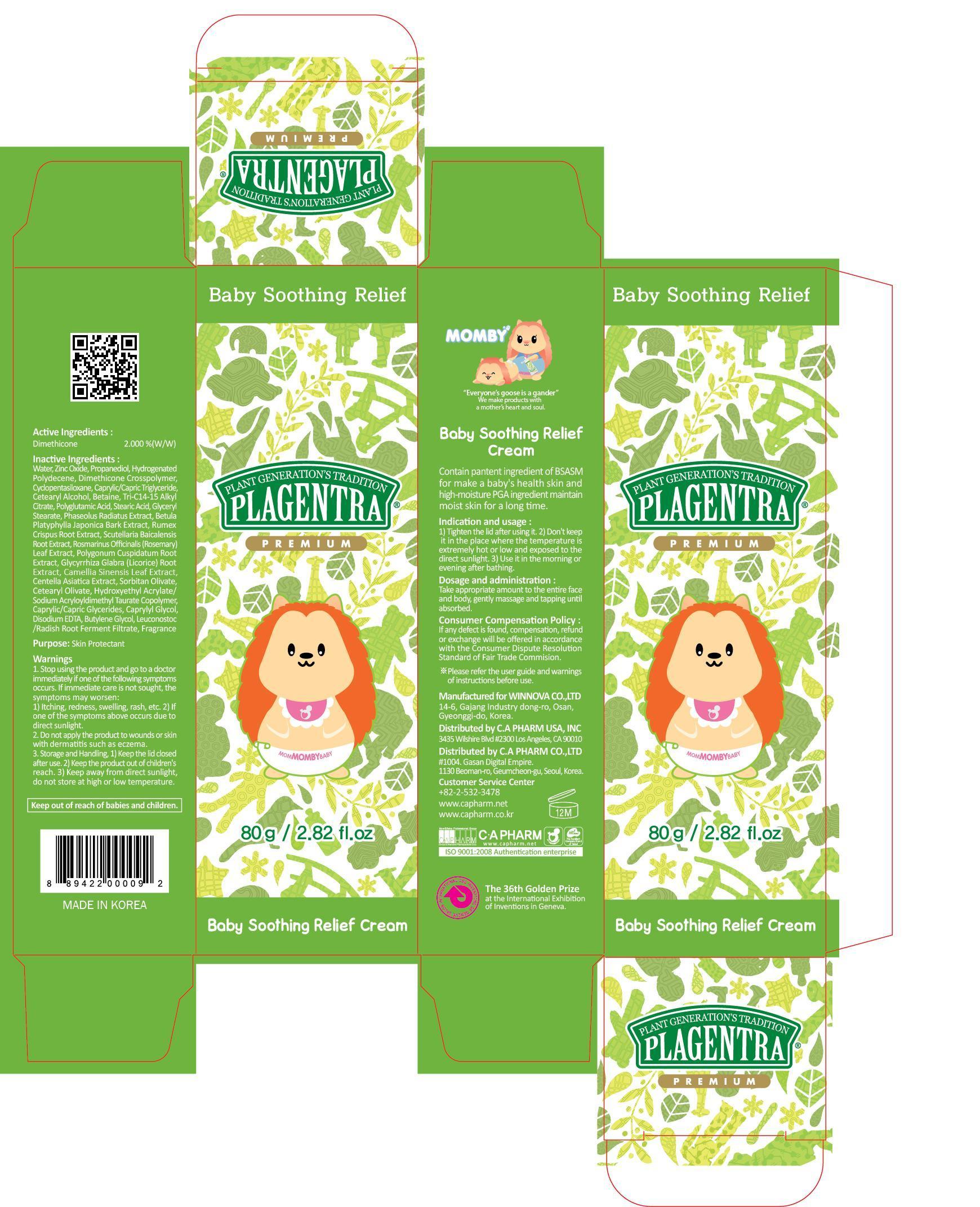 DRUG LABEL: PLAGENTRA BABY SOOTHING RELIEF
NDC: 68988-100 | Form: CREAM
Manufacturer: C.A Pharm Co., Ltd.
Category: otc | Type: HUMAN OTC DRUG LABEL
Date: 20141208

ACTIVE INGREDIENTS: Dimethicone 1.6 g/80 g
INACTIVE INGREDIENTS: Water; Zinc Oxide

ACTIVE INGREDIENT

Active Ingredient: Dimethicone 2%

INACTIVE INGREDIENT

Inactive Ingredients:
Water, Zinc Oxide, Propanediol, Hydrogenated Polydecene, Dimethicone Crosspolymer, Cyclopentasiloxane, Caprylic/Capric Triglyceride, Cetearyl Alcohol, Betaine, Tri-C14-15 Alkyl Citrate, Polyglutamic Acid, Stearic Acid, Glyceryl Stearate, Phaseolus Radiatus Extract, Betula Platyphylla Japonica Bark Extract, Rumex Crispus Root Extract, Scutellaria Baicalensis Root Extract, Rosmarinus Officinalis (Rosemary) Leaf Extract, Polygonum Cuspidatum Root Extract, Glycyrrhiza Glabra (Licorice) Root Extract, Camellia Sinensis Leaf Extract, Centella Asiatica Extract, Sorbitan Olivate, Cetearyl Olivate, Hydroxyethyl Acrylate/Sodium Acryloyldimethyl Taurate Copolymer, Caprylic/Capric Glycerides, Caprylyl Glycol, Disodium EDTA, Butylene Glycol, Leuconostoc/Radish Root Ferment Filtrate, Fragrance

PURPOSE

Purpose: Skin Portectant

WARNINGS

1. Stop using the product and go to a doctor immediately if one of the following symptoms occurs. If immediate care is not sought, the symptoms may worsen :
1) Itching, redness, swelling, rash, etc. 2) If one of the symptoms above occurs due to direct sunlight.
2. Do not apply the product to wounds or skin with dermatitis such as eczema.
3. Storage and Handling, 1) Keep the lid closed after use. 2) Keep the product out of children's reach. 3) Keep away from direct sunlight, do not store at high or low temperature.
4. It contains AHA. If it is your first time to use this product, take a small amount and gently apply to the skin to check if it cause andy trouble to your skin.

KEEP OUT OF REACH OF CHILDREN

Keep out of reach of babies and children.

INDICATIONS & USAGE

Indication and usage:
1) Tighten the lid after using it.
2) Don't keep it in the place where the temperature is extremely hot or low and exposed to the direct sunlight.
3) Use it in the morning or evening after shower.

DOSAGE & ADMINISTRATION

Dosage and administration:
Take appropriate amount to the entire face and body, gently massage and tapping until absorbed.